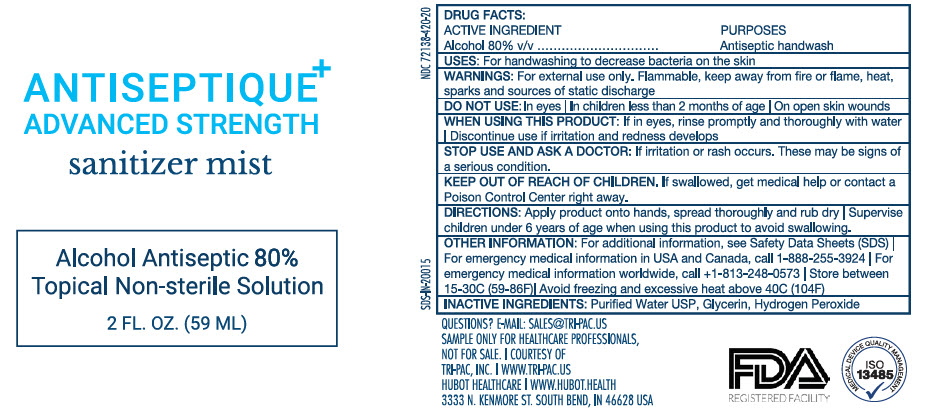 DRUG LABEL: Antiseptique Advance Strength
NDC: 72138-420 | Form: SPRAY
Manufacturer: Hubot Healthcare LLC
Category: otc | Type: HUMAN OTC DRUG LABEL
Date: 20200325

ACTIVE INGREDIENTS: ALCOHOL 80 mL/100 mL
INACTIVE INGREDIENTS: Water; Glycerin; Hydrogen Peroxide

Antiseptique Advance Strength

Drug Facts

Active ingredient

Ethyl Alcohol 80% v/v

Purposes

Antiseptic handwash

Uses

Hand sanitizer to help reduce bacteria that potentially can cause disease. For use when soap and water are not available.

Warnings

- For external use only
- Flammable, keep away from heat or flame.

Do not use

- In eyes | on children less than 2 months old | on open skin wounds

When using this product

- Keep out of eyes, ears and mouth. In case of contact with eyes, rinse eyes thoroughly with water.

Stop use and ask a doctor if skin irritation or rash occurs. There may be signs of a serious conditions.

Keep out of reach of children. If swallowed, get medical help or contact a Poison Control Center right away.

Directions

- Place enough product on hands to cover all surfaces. Rub hands together until dry. Supervise children under 6 years of age when using this product to avoid swallowing.

Other Information

- Store between 15-30°C (59-86°F), Avoid freezing and excessive heat above 40°C (104°F)

Inactive Ingredients

Purified Water USP, Glycerin, Hydrogen Peroxide

Questions?

Email: sales@tri-pac.us

PRINCIPAL DISPLAY PANEL - 59 ML Bottle Label

ANTISEPTIQUE^+
ADVANCED STRENGTH
sanitizer mist

Alcohol Antiseptic 80%
Topical Non-sterile Solution

2 FL. OZ. (59 ML)